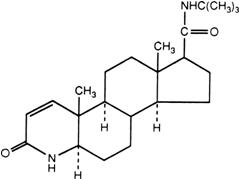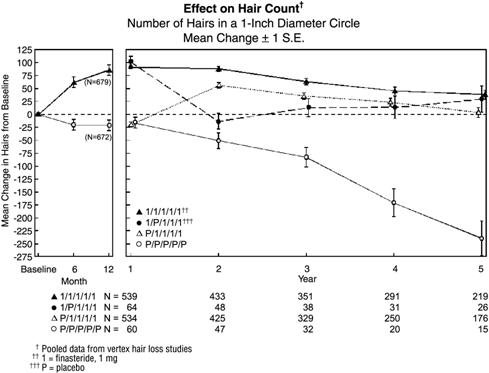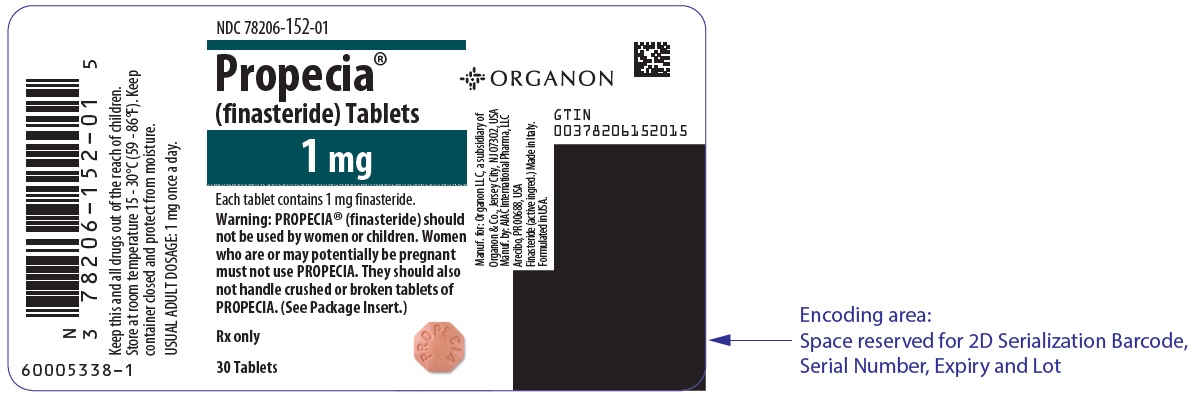 DRUG LABEL: PROPECIA
NDC: 78206-152 | Form: TABLET, FILM COATED
Manufacturer: Organon LLC
Category: prescription | Type: HUMAN PRESCRIPTION DRUG LABEL
Date: 20241014

ACTIVE INGREDIENTS: FINASTERIDE 1 mg/1 1
INACTIVE INGREDIENTS: LACTOSE MONOHYDRATE; MICROCRYSTALLINE CELLULOSE; STARCH, CORN; SODIUM STARCH GLYCOLATE TYPE A POTATO; HYPROMELLOSE, UNSPECIFIED; HYDROXYPROPYL CELLULOSE (1600000 WAMW); TITANIUM DIOXIDE; MAGNESIUM STEARATE; TALC; DOCUSATE SODIUM; FERRIC OXIDE YELLOW; FERRIC OXIDE RED

HIGHLIGHTS OF PRESCRIBING INFORMATION

These highlights do not include all the information needed to use PROPECIA safely and effectively. See full prescribing information for PROPECIA.
PROPECIA® (finasteride) tablets for oral use
Initial U.S. Approval: 1992

1 INDICATIONS AND USAGE

- PROPECIA is a 5α-reductase inhibitor indicated for the treatment of male pattern hair loss (androgenetic alopecia) in MEN ONLY (1).
- PROPECIA is not indicated for use in women (1, 4, 5.1).

2 DOSAGE AND ADMINISTRATION

- PROPECIA may be administered with or without meals (2).
- One tablet (1 mg) taken once daily (2).
- In general, daily use for three months or more is necessary before benefit is observed (2).

3 DOSAGE FORMS AND STRENGTHS

1 mg tablets (3).

4 CONTRAINDICATIONS

- Pregnancy (4, 5.1, 8.1, 16).
- Hypersensitivity to any components of this product (4).

5 WARNINGS AND PRECAUTIONS

- PROPECIA is not indicated for use in women or pediatric patients (5.1, 5.4).
- Women should not handle crushed or broken PROPECIA tablets when they are pregnant or may potentially be pregnant due to potential risk to a male fetus (5.1, 8.1, 16).
- PROPECIA causes a decrease in serum PSA levels. Any confirmed increase in PSA while on PROPECIA may signal the presence of prostate cancer and should be evaluated, even if those values are still within the normal range for men not taking a 5α-reductase inhibitor (5.2).
- 5α-reductase inhibitors may increase the risk of high-grade prostate cancer (5.3, 6.1).

6 ADVERSE REACTIONS

The most common adverse reactions, reported in ≥1% of patients treated with PROPECIA and greater than in patients treated with placebo are: decreased libido, erectile dysfunction and ejaculation disorder (6.1).

To report SUSPECTED ADVERSE REACTIONS, contact Organon LLC, a subsidiary of Organon & Co., at 1-844-674-3200 or FDA at 1-800-FDA-1088 or www.fda.gov/medwatch.

FULL PRESCRIBING INFORMATION

1 INDICATIONS AND USAGE

PROPECIA® is indicated for the treatment of male pattern hair loss (androgenetic alopecia) in MEN ONLY.

Efficacy in bitemporal recession has not been established.

PROPECIA is not indicated for use in women.

2 DOSAGE AND ADMINISTRATION

PROPECIA may be administered with or without meals.

The recommended dose of PROPECIA is one tablet (1 mg) taken once daily.

In general, daily use for three months or more is necessary before benefit is observed. Continued use is recommended to sustain benefit, which should be re-evaluated periodically. Withdrawal of treatment leads to reversal of effect within 12 months.

3 DOSAGE FORMS AND STRENGTHS

PROPECIA tablets (1 mg) are tan, octagonal, film-coated convex tablets with "stylized P" logo on one side and PROPECIA on the other.

4 CONTRAINDICATIONS

PROPECIA is contraindicated in the following:

- Pregnancy. Finasteride use is contraindicated in women when they are or may potentially be pregnant. Because of the ability of Type II 5α-reductase inhibitors to inhibit the conversion of testosterone to 5α-dihydrotestosterone (DHT), finasteride may cause abnormalities of the external genitalia of a male fetus of a pregnant woman who receives finasteride. If this drug is used during pregnancy, or if pregnancy occurs while taking this drug, the pregnant woman should be apprised of the potential hazard to the male fetus. [See Warnings and Precautions (5.1), Use in Specific Populations (8.1), How Supplied/Storage and Handling (16) and Patient Counseling Information (17).] In female rats, low doses of finasteride administered during pregnancy have produced abnormalities of the external genitalia in male offspring.
- Hypersensitivity to any component of this medication.

5 WARNINGS AND PRECAUTIONS

5.1 Exposure of Women — Risk to Male Fetus

PROPECIA is not indicated for use in women. Women should not handle crushed or broken PROPECIA tablets when they are pregnant or may potentially be pregnant because of the possibility of absorption of finasteride and the subsequent potential risk to a male fetus. PROPECIA tablets are coated and will prevent contact with the active ingredient during normal handling, provided that the tablets have not been broken or crushed. [See Indications and Usage (1), Contraindications (4), Use in Specific Populations (8.1), How Supplied/Storage and Handling (16) and Patient Counseling Information (17).]

5.2 Effects on Prostate Specific Antigen (PSA)

In clinical studies with PROPECIA (finasteride, 1 mg) in men 18-41 years of age, the mean value of serum prostate specific antigen (PSA) decreased from 0.7 ng/mL at baseline to 0.5 ng/mL at Month 12. Further, in clinical studies with PROSCAR (finasteride, 5 mg) when used in older men who have benign prostatic hyperplasia (BPH), PSA levels are decreased by approximately 50%. Other studies with PROSCAR showed it may also cause decreases in serum PSA in the presence of prostate cancer. These findings should be taken into account for proper interpretation of serum PSA when evaluating men treated with finasteride. Any confirmed increase from the lowest PSA value while on PROPECIA may signal the presence of prostate cancer and should be evaluated, even if PSA levels are still within the normal range for men not taking a 5α-reductase inhibitor. Non-compliance to therapy with PROPECIA may also affect PSA test results.

5.3 Increased Risk of High-Grade Prostate Cancer with 5α-Reductase Inhibitors

Men aged 55 and over with a normal digital rectal examination and PSA ≤3.0 ng/mL at baseline taking finasteride 5 mg/day (5 times the dose of PROPECIA) in the 7-year Prostate Cancer Prevention Trial (PCPT) had an increased risk of Gleason score 8-10 prostate cancer (finasteride 1.8% vs placebo 1.1%). [See Adverse Reactions (6.1).] Similar results were observed in a 4-year placebo-controlled clinical trial with another 5α-reductase inhibitor (dutasteride, AVODART) (1% dutasteride vs 0.5% placebo). 5α-reductase inhibitors may increase the risk of development of high-grade prostate cancer. Whether the effect of 5α-reductase inhibitors to reduce prostate volume, or study-related factors, impacted the results of these studies has not been established.

5.4 Pediatric Patients

PROPECIA is not indicated for use in pediatric patients [see Use in Specific Populations (8.4)].

6 ADVERSE REACTIONS

6.1 Clinical Trials Experience

Because clinical trials are conducted under widely varying conditions, adverse reaction rates observed in the clinical trials of a drug cannot be directly compared to rates in the clinical trials of another drug and may not reflect the rates observed in clinical practice.

Clinical Studies for PROPECIA (finasteride 1 mg) in the Treatment of Male Pattern Hair Loss

In three controlled clinical trials for PROPECIA of 12-month duration, 1.4% of patients taking PROPECIA (n=945) were discontinued due to adverse experiences that were considered to be possibly, probably or definitely drug-related (1.6% for placebo; n=934).

Clinical adverse experiences that were reported as possibly, probably or definitely drug-related in ≥1% of patients treated with PROPECIA or placebo are presented in Table 1.

TABLE 1: Drug-Related Adverse Experiences for PROPECIA (finasteride 1 mg) in Year 1 (%) MALE PATTERN HAIR LOSS
 | PROPECIA N=945 | Placebo N=934
Decreased Libido | 1.8 | 1.3
Erectile Dysfunction | 1.3 | 0.7
Ejaculation Disorder (Decreased Volume of Ejaculate) | 1.2 (0.8) | 0.7 (0.4)
Discontinuation due to drug-related sexual adverse experiences | 1.2 | 0.9

Integrated analysis of clinical adverse experiences showed that during treatment with PROPECIA, 36 (3.8%) of 945 men had reported one or more of these adverse experiences as compared to 20 (2.1%) of 934 men treated with placebo (p=0.04). Resolution occurred in men who discontinued therapy with PROPECIA due to these side effects and in most of those who continued therapy. The incidence of each of the above adverse experiences decreased to ≤0.3% by the fifth year of treatment with PROPECIA.

In a study of finasteride 1 mg daily in healthy men, a median decrease in ejaculate volume of 0.3 mL (-11%) compared with 0.2 mL (-8%) for placebo was observed after 48 weeks of treatment. Two other studies showed that finasteride at 5 times the dosage of PROPECIA (5 mg daily) produced significant median decreases of approximately 0.5 mL (-25%) compared to placebo in ejaculate volume, but this was reversible after discontinuation of treatment.

In the clinical studies with PROPECIA, the incidences for breast tenderness and enlargement, hypersensitivity reactions, and testicular pain in finasteride-treated patients were not different from those in patients treated with placebo.

Controlled Clinical Trials and Long-Term Open Extension Studies for PROSCAR® (finasteride 5 mg) and AVODART (dutasteride) in the Treatment of Benign Prostatic Hyperplasia

In the PROSCAR Long-Term Efficacy and Safety Study (PLESS), a 4-year controlled clinical study, 3040 patients between the ages of 45 and 78 with symptomatic BPH and an enlarged prostate were evaluated for safety over a period of 4 years (1524 on PROSCAR 5 mg/day and 1516 on placebo). 3.7% (57 patients) treated with PROSCAR 5 mg and 2.1% (32 patients) treated with placebo discontinued therapy as a result of adverse reactions related to sexual function, which are the most frequently reported adverse reactions.

Table 2 presents the only clinical adverse reactions considered possibly, probably or definitely drug related by the investigator, for which the incidence on PROSCAR was ≥1% and greater than placebo over the 4 years of the study. In years 2-4 of the study, there was no significant difference between treatment groups in the incidences of impotence, decreased libido and ejaculation disorder.

TABLE 2: Drug-Related Adverse Experiences for PROSCAR (finasteride 5 mg) BENIGN PROSTATIC HYPERPLASIA
 | Year 1 (%) |  | Years 2, 3 and 4 [Combined Years 2-4] (%)
 | Finasteride 5 mg | Placebo | Finasteride 5 mg | Placebo
Impotence | 8.1 | 3.7 | 5.1 | 5.1
Decreased Libido | 6.4 | 3.4 | 2.6 | 2.6
Decreased Volume of Ejaculate | 3.7 | 0.8 | 1.5 | 0.5
Ejaculation Disorder | 0.8 | 0.1 | 0.2 | 0.1
Breast Enlargement | 0.5 | 0.1 | 1.8 | 1.1
Breast Tenderness | 0.4 | 0.1 | 0.7 | 0.3
Rash | 0.5 | 0.2 | 0.5 | 0.1
N = 1524 and 1516, finasteride vs placebo, respectively

The adverse experience profiles in the 1-year, placebo-controlled, Phase III BPH studies and the 5-year open extensions with PROSCAR 5 mg and PLESS were similar.

There is no evidence of increased sexual adverse experiences with increased duration of treatment with PROSCAR 5 mg. New reports of drug-related sexual adverse experiences decreased with duration of therapy.

During the 4- to 6-year placebo- and comparator-controlled Medical Therapy of Prostatic Symptoms (MTOPS) study that enrolled 3047 men, there were 4 cases of breast cancer in men treated with PROSCAR but no cases in men not treated with PROSCAR. During the 4-year placebo-controlled PLESS study that enrolled 3040 men, there were 2 cases of breast cancer in placebo-treated men, but no cases were reported in men treated with PROSCAR.

During the 7-year placebo-controlled Prostate Cancer Prevention Trial (PCPT) that enrolled 18,882 men, there was 1 case of breast cancer in men treated with PROSCAR, and 1 case of breast cancer in men treated with placebo. The relationship between long-term use of finasteride and male breast neoplasia is currently unknown.

The PCPT trial was a 7-year randomized, double-blind, placebo-controlled trial that enrolled 18,882 healthy men ≥55 years of age with a normal digital rectal examination and a PSA ≤3.0 ng/mL. Men received either PROSCAR (finasteride 5 mg) or placebo daily. Patients were evaluated annually with PSA and digital rectal exams. Biopsies were performed for elevated PSA, an abnormal digital rectal exam, or the end of study. The incidence of Gleason score 8-10 prostate cancer was higher in men treated with finasteride (1.8%) than in those treated with placebo (1.1%). In a 4-year placebo-controlled clinical trial with another 5α-reductase inhibitor [AVODART (dutasteride)], similar results for Gleason score 8-10 prostate cancer were observed (1% dutasteride vs 0.5% placebo). The clinical significance of these findings with respect to use of PROPECIA by men is unknown.

No clinical benefit has been demonstrated in patients with prostate cancer treated with PROSCAR. PROSCAR is not approved to reduce the risk of developing prostate cancer.

Sexual Function Questionnaire

A sexual function questionnaire was self-administered by patients participating in the two vertex baldness trials to detect more subtle changes in sexual function. At Month 12, statistically significant differences in favor of placebo were found in 3 of 4 domains (sexual interest, erections, and perception of sexual problems). However, no significant difference was seen in the question on overall satisfaction with sex life.

In one of the two vertex baldness studies, patients were questioned on non-scalp body hair growth. PROPECIA did not appear to affect non-scalp body hair.

6.2 Postmarketing Experience

The following adverse reactions have been identified during post approval use of PROPECIA. Because these reactions are reported voluntarily from a population of uncertain size, it is not always possible to reliably estimate their frequency or establish a causal relationship to drug exposure:

Hypersensitivity Reaction: hypersensitivity reactions such as rash, pruritus, urticaria, and angioedema (including swelling of the lips, tongue, throat, and face);

Reproductive System: sexual dysfunction that continued after discontinuation of treatment, including erectile dysfunction, libido disorders, ejaculation disorders, and orgasm disorders; male infertility and/or poor seminal quality (normalization or improvement of seminal quality has been reported after discontinuation of finasteride); testicular pain; hematospermia.

Neoplasms: male breast cancer;

Breast disorders: breast tenderness and enlargement;

Nervous System/Psychiatric: depression, suicidal ideation and behavior.

7 DRUG INTERACTIONS

7.1 Cytochrome P450-Linked Drug Metabolizing Enzyme System

No drug interactions of clinical importance have been identified. Finasteride does not appear to affect the cytochrome P450-linked drug-metabolizing enzyme system. Compounds that have been tested in man include antipyrine, digoxin, propranolol, theophylline, and warfarin and no clinically meaningful interactions were found.

7.2 Other Concomitant Therapy

Although specific interaction studies were not performed, finasteride doses of 1 mg or more were concomitantly used in clinical studies with acetaminophen, acetylsalicylic acid, α-blockers, analgesics, angiotensin-converting enzyme (ACE) inhibitors, anticonvulsants, benzodiazepines, beta blockers, calcium-channel blockers, cardiac nitrates, diuretics, H2 antagonists, HMG-CoA reductase inhibitors, prostaglandin synthetase inhibitors (also referred to as NSAIDs), and quinolone anti-infectives without evidence of clinically significant adverse interactions.

8 USE IN SPECIFIC POPULATIONS

8.1 Pregnancy

TERATOGENIC EFFECTS

Pregnancy Category X [see Contraindications (4)]. PROPECIA is contraindicated for use in women who are or may become pregnant. PROPECIA is a Type II 5α-reductase inhibitor that prevents conversion of testosterone to 5α-dihydrotestosterone (DHT), a hormone necessary for normal development of male genitalia. In animal studies, finasteride caused abnormal development of external genitalia in male fetuses. If this drug is used during pregnancy, or if the patient becomes pregnant while taking this drug, the patient should be apprised of the potential hazard to the male fetus.

Abnormal male genital development is an expected consequence when conversion of testosterone to 5α-dihydrotestosterone (DHT) is inhibited by 5α-reductase inhibitors. These outcomes are similar to those reported in male infants with genetic 5α-reductase deficiency. Women could be exposed to finasteride through contact with crushed or broken PROPECIA tablets or semen from a male partner taking PROPECIA. With regard to finasteride exposure through the skin, PROPECIA tablets are coated and will prevent skin contact with finasteride during normal handling if the tablets have not been crushed or broken. Women who are pregnant or may become pregnant should not handle crushed or broken PROPECIA tablets because of possible exposure of a male fetus. If a pregnant woman comes in contact with crushed or broken PROPECIA tablets, the contact area should be washed immediately with soap and water. With regard to potential finasteride exposure through semen, a study has been conducted in men receiving PROPECIA 1 mg/day that measured finasteride concentrations in semen [see Clinical Pharmacology (12.3)].

In an embryo-fetal development study, pregnant rats received finasteride during the period of major organogenesis (gestation days 6 to 17). At maternal doses of oral finasteride approximately 1 to 684 times the recommended human dose (RHD) of 1 mg/day (based on AUC at animal doses of 0.1 to 100 mg/kg/day) there was a dose-dependent increase in hypospadias that occurred in 3.6 to 100% of male offspring. Exposure multiples were estimated using data from nonpregnant rats. Days 16 to 17 of gestation is a critical period in male fetal rats for differentiation of the external genitalia. At oral maternal doses approximately 0.2 times the RHD (based on AUC at animal dose of 0.03 mg/kg/day), male offspring had decreased prostatic and seminal vesicular weights, delayed preputial separation and transient nipple development. Decreased anogenital distance occurred in male offspring of pregnant rats that received approximately 0.02 times the RHD (based on AUC at animal dose of 0.003 mg/kg/day). No abnormalities were observed in female offspring exposed to any dose of finasteride in utero.

No developmental abnormalities were observed in the offspring of untreated females mated with finasteride-treated male rats that received approximately 488 times the RHD (based on AUC at animal dose of 80 mg/kg/day). Slightly decreased fertility was observed in male offspring after administration of about 20 times the RHD (based on AUC at animal dose of 3 mg/kg/day) to female rats during late gestation and lactation. No effects on fertility were seen in female offspring under these conditions.

No evidence of male external genital malformations or other abnormalities were observed in rabbit fetuses exposed to finasteride during the period of major organogenesis (gestation days 6-18) at maternal doses up to 100 mg/kg/day (finasteride exposure levels were not measured in rabbits). However, this study may not have included the critical period for finasteride effects on development of male external genitalia in the rabbit.

The fetal effects of maternal finasteride exposure during the period of embryonic and fetal development were evaluated in the rhesus monkey (gestation days 20-100), in a species and development period more predictive of specific effects in humans than the studies in rats and rabbits. Intravenous administration of finasteride to pregnant monkeys at doses as high as 800 ng/day (estimated maximal blood concentration of 1.86 ng/mL or about 930 times the highest estimated exposure of pregnant women to finasteride from semen of men taking 1 mg/day) resulted in no abnormalities in male fetuses. In confirmation of the relevance of the rhesus model for human fetal development, oral administration of a dose of finasteride (2 mg/kg/day or approximately 120,000 times the highest estimated blood levels of finasteride from semen of men taking 1 mg/day) to pregnant monkeys resulted in external genital abnormalities in male fetuses. No other abnormalities were observed in male fetuses and no finasteride-related abnormalities were observed in female fetuses at any dose.

8.3 Nursing Mothers

PROPECIA is not indicated for use in women.

It is not known whether finasteride is excreted in human milk.

8.4 Pediatric Use

PROPECIA is not indicated for use in pediatric patients.

Safety and effectiveness in pediatric patients have not been established.

8.5 Geriatric Use

Clinical efficacy studies with PROPECIA did not include subjects aged 65 and over. Based on the pharmacokinetics of finasteride 5 mg, no dosage adjustment is necessary in the elderly for PROPECIA [see Clinical Pharmacology (12.3)]. However, the efficacy of PROPECIA in the elderly has not been established.

8.6 Hepatic Impairment

Caution should be exercised in the administration of PROPECIA in those patients with liver function abnormalities, as finasteride is metabolized extensively in the liver [see Clinical Pharmacology (12.3)].

8.7 Renal Impairment

No dosage adjustment is necessary in patients with renal impairment [see Clinical Pharmacology (12.3)].

10 OVERDOSAGE

In clinical studies, single doses of finasteride up to 400 mg and multiple doses of finasteride up to 80 mg/day for three months did not result in adverse reactions. Until further experience is obtained, no specific treatment for an overdose with finasteride can be recommended.

Significant lethality was observed in male and female mice at single oral doses of 1500 mg/m^2 (500 mg/kg) and in female and male rats at single oral doses of 2360 mg/m^2 (400 mg/kg) and 5900 mg/m^2 (1000 mg/kg), respectively.

11 DESCRIPTION

PROPECIA (finasteride) tablets contain finasteride as the active ingredient. Finasteride, a synthetic 4-azasteroid compound, is a specific inhibitor of steroid Type II 5α-reductase, an intracellular enzyme that converts the androgen testosterone into 5α-dihydrotestosterone (DHT).

The chemical name of finasteride is N-tert-Butyl-3-oxo-4-aza-5α-androst-1-ene-17β-carboxamide. The empirical formula of finasteride is C23H36N2O2 and its molecular weight is 372.55. Its structural formula is:

Finasteride is a white crystalline powder with a melting point near 250°C. It is freely soluble in chloroform and in lower alcohol solvents but is practically insoluble in water.

PROPECIA (finasteride) tablets are film-coated tablets for oral administration. Each tablet contains 1 mg of finasteride and the following inactive ingredients: lactose monohydrate, microcrystalline cellulose, pregelatinized starch, sodium starch glycolate, hydroxypropyl methylcellulose, hydroxypropyl cellulose, titanium dioxide, magnesium stearate, talc, docusate sodium, yellow ferric oxide, and red ferric oxide.

12 CLINICAL PHARMACOLOGY

12.1 Mechanism of Action

Finasteride is a competitive and specific inhibitor of Type II 5α-reductase, an intracellular enzyme that converts the androgen testosterone into DHT. Two distinct isozymes are found in mice, rats, monkeys, and humans: Type I and II. Each of these isozymes is differentially expressed in tissues and developmental stages. In humans, Type I 5α-reductase is predominant in the sebaceous glands of most regions of skin, including scalp, and liver. Type I 5α-reductase is responsible for approximately one-third of circulating DHT. The Type II 5α-reductase isozyme is primarily found in prostate, seminal vesicles, epididymides, and hair follicles as well as liver, and is responsible for two-thirds of circulating DHT.

In humans, the mechanism of action of finasteride is based on its preferential inhibition of the Type II isozyme. Using native tissues (scalp and prostate), in vitro binding studies examining the potential of finasteride to inhibit either isozyme revealed a 100-fold selectivity for the human Type II 5α-reductase over Type I isozyme (IC50=500 and 4.2 nM for Type I and II, respectively). For both isozymes, the inhibition by finasteride is accompanied by reduction of the inhibitor to dihydrofinasteride and adduct formation with NADP+. The turnover for the enzyme complex is slow (t1/2 approximately 30 days for the Type II enzyme complex and 14 days for the Type I complex). Inhibition of Type II 5α-reductase blocks the peripheral conversion of testosterone to DHT, resulting in significant decreases in serum and tissue DHT concentrations.

In men with male pattern hair loss (androgenetic alopecia), the balding scalp contains miniaturized hair follicles and increased amounts of DHT compared with hairy scalp. Administration of finasteride decreases scalp and serum DHT concentrations in these men. The relative contributions of these reductions to the treatment effect of finasteride have not been defined. By this mechanism, finasteride appears to interrupt a key factor in the development of androgenetic alopecia in those patients genetically predisposed.

12.2 Pharmacodynamics

Finasteride produces a rapid reduction in serum DHT concentration, reaching 65% suppression within 24 hours of oral dosing with a 1-mg tablet. Mean circulating levels of testosterone and estradiol were increased by approximately 15% as compared to baseline, but these remained within the physiologic range.

Finasteride has no affinity for the androgen receptor and has no androgenic, antiandrogenic, estrogenic, antiestrogenic, or progestational effects. The relationship between these pharmacodynamic activities and the mechanisms(s) by which PROPECIA exerts its clinical effect is unknown. In studies with finasteride, no clinically meaningful changes in luteinizing hormone (LH), follicle-stimulating hormone (FSH) or prolactin were detected. In healthy volunteers, treatment with finasteride did not alter the response of LH and FSH to gonadotropin-releasing hormone indicating that the hypothalamic-pituitary-testicular axis was not affected. Finasteride had no effect on circulating levels of cortisol, thyroid-stimulating hormone, or thyroxine, nor did it affect the plasma lipid profile (e.g., total cholesterol, low-density lipoproteins, high-density lipoproteins and triglycerides) or bone mineral density.

12.3 Pharmacokinetics

Absorption

In a study in 15 healthy young male subjects, the mean bioavailability of finasteride 1-mg tablets was 65% (range 26-170%), based on the ratio of area under the curve (AUC) relative to an intravenous (IV) reference dose. At steady state following dosing with 1 mg/day (n=12), maximum finasteride plasma concentration averaged 9.2 ng/mL (range, 4.9-13.7 ng/mL) and was reached 1 to 2 hours postdose; AUC(0-24 hr) was 53 ng∙hr/mL (range, 20-154 ng∙hr/mL). Bioavailability of finasteride was not affected by food.

Distribution

Mean steady-state volume of distribution was 76 liters (range, 44-96 liters; n=15). Approximately 90% of circulating finasteride is bound to plasma proteins. There is a slow accumulation phase for finasteride after multiple dosing.

Finasteride has been found to cross the blood-brain barrier.

Semen levels have been measured in 35 men taking finasteride 1 mg/day for 6 weeks. In 60% (21 of 35) of the samples, finasteride levels were undetectable (<0.2 ng/mL). The mean finasteride level was 0.26 ng/mL and the highest level measured was 1.52 ng/mL. Using the highest semen level measured and assuming 100% absorption from a 5-mL ejaculate per day, human exposure through vaginal absorption would be up to 7.6 ng per day, which is 650-fold less than the dose of finasteride (5 µg) that had no effect on circulating DHT levels in men. [See Use in Specific Populations (8.1).]

Metabolism

Finasteride is extensively metabolized in the liver, primarily via the cytochrome P450 3A4 enzyme subfamily. Two metabolites, the t-butyl side chain monohydroxylated and monocarboxylic acid metabolites, have been identified that possess no more than 20% of the 5α-reductase inhibitory activity of finasteride.

Excretion

Following intravenous infusion in healthy young subjects (n=15), mean plasma clearance of finasteride was 165 mL/min (range, 70-279 mL/min). Mean terminal half-life in plasma was 4.5 hours (range, 3.3-13.4 hours; n=12). Following an oral dose of ^14C-finasteride in man (n=6), a mean of 39% (range, 32-46%) of the dose was excreted in the urine in the form of metabolites; 57% (range, 51-64%) was excreted in the feces.

Mean terminal half-life is approximately 5-6 hours in men 18-60 years of age and 8 hours in men more than 70 years of age.

TABLE 3: Mean (SD) Pharmacokinetic Parameters in Healthy Men (ages 18-26)
 | Mean (± SD) n=15
Bioavailability | 65% (26-170%) [Range]
Clearance (mL/min) | 165 (55)
Volume of Distribution (L) | 76 (14)

TABLE 4: Mean (SD) Noncompartmental Pharmacokinetic Parameters After Multiple Doses of 1 mg/day in Healthy Men (ages 19-42)
 | Mean (± SD) (n=12)
AUC (ng∙hr/mL) | 53 (33.8)
Peak Concentration (ng/mL) | 9.2 (2.6)
Time to Peak (hours) | 1.3 (0.5)
Half-Life (hours) [First-dose values; all other parameters are last-dose values] | 4.5 (1.6)

Renal Impairment

No dosage adjustment is necessary in patients with renal impairment. In patients with chronic renal impairment, with creatinine clearances ranging from 9.0 to 55 mL/min, AUC, maximum plasma concentration, half-life, and protein binding after a single dose of ^14C-finasteride were similar to those obtained in healthy volunteers. Urinary excretion of metabolites was decreased in patients with renal impairment. This decrease was associated with an increase in fecal excretion of metabolites. Plasma concentrations of metabolites were significantly higher in patients with renal impairment (based on a 60% increase in total radioactivity AUC). However, finasteride has been tolerated in men with normal renal function receiving up to 80 mg/day for 12 weeks where exposure of these patients to metabolites would presumably be much greater.

Hepatic Impairment

The effect of hepatic impairment on finasteride pharmacokinetics has not been studied. Caution should be used in the administration of PROPECIA in patients with liver function abnormalities, as finasteride is metabolized extensively in the liver.

13 NONCLINICAL TOXICOLOGY

13.1 Carcinogenesis, Mutagenesis, Impairment of Fertility

No evidence of a tumorigenic effect was observed in a 24-month study in Sprague-Dawley rats receiving doses of finasteride up to 160 mg/kg/day in males and 320 mg/kg/day in females. These doses produced respective systemic exposure in rats of 888 and 2192 times those observed in man receiving the recommended human dose of 1 mg/day. All exposure calculations were based on calculated AUC(0-24 hr) for animals and mean AUC(0-24 hr) for man (0.05 µg∙hr/mL).

In a 19-month carcinogenicity study in CD-1 mice, a statistically significant (p≤0.05) increase in the incidence of testicular Leydig cell adenomas was observed at 1824 times the human exposure (250 mg/kg/day). In mice at 184 times the human exposure, estimated (25 mg/kg/day) and in rats at 312 times the human exposure (≥40 mg/kg/day) an increase in the incidence of Leydig cell hyperplasia was observed. A positive correlation between the proliferative changes in the Leydig cells and an increase in serum LH levels (2- to 3-fold above control) has been demonstrated in both rodent species treated with high doses of finasteride. No drug-related Leydig cell changes were seen in either rats or dogs treated with finasteride for 1 year at 240 and 2800 times (20 mg/kg/day and 45 mg/kg/day, respectively), or in mice treated for 19 months at 18.4 times the human exposure, estimated (2.5 mg/kg/day).

No evidence of mutagenicity was observed in an in vitro bacterial mutagenesis assay, a mammalian cell mutagenesis assay, or in an in vitro alkaline elution assay. In an in vitro chromosome aberration assay, using Chinese hamster ovary cells, there was a slight increase in chromosome aberrations. In an in vivo chromosome aberration assay in mice, no treatment-related increase in chromosome aberration was observed with finasteride at the maximum tolerated dose of 250 mg/kg/day (1824 times the human exposure) as determined in the carcinogenicity studies.

In sexually mature male rabbits treated with finasteride at 4344 times the human exposure (80 mg/kg/day) for up to 12 weeks, no effect on fertility, sperm count, or ejaculate volume was seen. In sexually mature male rats treated with 488 times the human exposure (80 mg/kg/day), there were no significant effects on fertility after 6 or 12 weeks of treatment; however, when treatment was continued for up to 24 or 30 weeks, there was an apparent decrease in fertility, fecundity, and an associated significant decrease in the weights of the seminal vesicles and prostate. All these effects were reversible within 6 weeks of discontinuation of treatment. No drug-related effect on testes or on mating performance has been seen in rats or rabbits. This decrease in fertility in finasteride-treated rats is secondary to its effect on accessory sex organs (prostate and seminal vesicles) resulting in failure to form a seminal plug. The seminal plug is essential for normal fertility in rats but is not relevant in man.

14 CLINICAL STUDIES

14.1 Studies in Men

The efficacy of PROPECIA was demonstrated in men (88% Caucasian) with mild to moderate androgenetic alopecia (male pattern hair loss) between 18 and 41 years of age. In order to prevent seborrheic dermatitis which might confound the assessment of hair growth in these studies, all men, whether treated with finasteride or placebo, were instructed to use a specified, medicated, tar-based shampoo (Neutrogena T/Gel® Shampoo) during the first 2 years of the studies.

There were three double-blind, randomized, placebo-controlled studies of 12-month duration. The two primary endpoints were hair count and patient self-assessment; the two secondary endpoints were investigator assessment and ratings of photographs. In addition, information was collected regarding sexual function (based on a self-administered questionnaire) and non-scalp body hair growth. The three studies were conducted in 1879 men with mild to moderate, but not complete, hair loss. Two of the studies enrolled men with predominantly mild to moderate vertex hair loss (n=1553). The third enrolled men having mild to moderate hair loss in the anterior mid-scalp area with or without vertex balding (n=326).

Studies in Men with Vertex Baldness

Of the men who completed the first 12 months of the two vertex baldness trials, 1215 elected to continue in double-blind, placebo-controlled, 12-month extension studies. There were 547 men receiving PROPECIA for both the initial study and first extension periods (up to 2 years of treatment) and 60 men receiving placebo for the same periods. The extension studies were continued for 3 additional years, with 323 men on PROPECIA and 23 on placebo entering the fifth year of the study.

In order to evaluate the effect of discontinuation of therapy, there were 65 men who received PROPECIA for the initial 12 months followed by placebo in the first 12-month extension period. Some of these men continued in additional extension studies and were switched back to treatment with PROPECIA, with 32 men entering the fifth year of the study. Lastly, there were 543 men who received placebo for the initial 12 months followed by PROPECIA in the first 12-month extension period. Some of these men continued in additional extension studies receiving PROPECIA, with 290 men entering the fifth year of the study (see Figure 1 below).

Hair counts were assessed by photographic enlargements of a representative area of active hair loss. In these two studies in men with vertex baldness, significant increases in hair count were demonstrated at 6 and 12 months in men treated with PROPECIA, while significant hair loss from baseline was demonstrated in those treated with placebo. At 12 months there was a 107-hair difference from placebo (p<0.001, PROPECIA [n=679] vs placebo [n=672]) within a 1-inch diameter circle (5.1 cm^2). Hair count was maintained in those men taking PROPECIA for up to 2 years, resulting in a 138-hair difference between treatment groups (p<0.001, PROPECIA [n=433] vs placebo [n=47]) within the same area. In men treated with PROPECIA, the maximum improvement in hair count compared to baseline was achieved during the first 2 years. Although the initial improvement was followed by a slow decline, hair count was maintained above baseline throughout the 5 years of the studies. Furthermore, because the decline in the placebo group was more rapid, the difference between treatment groups also continued to increase throughout the studies, resulting in a 277-hair difference (p<0.001, PROPECIA [n=219] vs placebo [n=15]) at 5 years (see Figure 1 below).

Patients who switched from placebo to PROPECIA (n=425) had a decrease in hair count at the end of the initial 12-month placebo period, followed by an increase in hair count after 1 year of treatment with PROPECIA. This increase in hair count was less (56 hairs above original baseline) than the increase (91 hairs above original baseline) observed after 1 year of treatment in men initially randomized to PROPECIA. Although the increase in hair count, relative to when therapy was initiated, was comparable between these two groups, a higher absolute hair count was achieved in patients who were started on treatment with PROPECIA in the initial study. This advantage was maintained through the remaining 3 years of the studies. A change of treatment from PROPECIA to placebo (n=48) at the end of the initial 12 months resulted in reversal of the increase in hair count 12 months later, at 24 months (see Figure 1 below).

At 12 months, 58% of men in the placebo group had further hair loss (defined as any decrease in hair count from baseline), compared with 14% of men treated with PROPECIA. In men treated for up to 2 years, 72% of men in the placebo group demonstrated hair loss, compared with 17% of men treated with PROPECIA. At 5 years, 100% of men in the placebo group demonstrated hair loss, compared with 35% of men treated with PROPECIA.

Figure 1

Patient self-assessment was obtained at each clinic visit from a self-administered questionnaire, which included questions on their perception of hair growth, hair loss, and appearance. This self-assessment demonstrated an increase in amount of hair, a decrease in hair loss, and improvement in appearance in men treated with PROPECIA. Overall improvement compared with placebo was seen as early as 3 months (p<0.05), with improvement maintained over 5 years.

Investigator assessment was based on a 7-point scale evaluating increases or decreases in scalp hair at each patient visit. This assessment showed significantly greater increases in hair growth in men treated with PROPECIA compared with placebo as early as 3 months (p<0.001). At 12 months, the investigators rated 65% of men treated with PROPECIA as having increased hair growth compared with 37% in the placebo group. At 2 years, the investigators rated 80% of men treated with PROPECIA as having increased hair growth compared with 47% of men treated with placebo. At 5 years, the investigators rated 77% of men treated with PROPECIA as having increased hair growth, compared with 15% of men treated with placebo.

An independent panel rated standardized photographs of the head in a blinded fashion based on increases or decreases in scalp hair using the same 7-point scale as the investigator assessment. At 12 months, 48% of men treated with PROPECIA had an increase as compared with 7% of men treated with placebo. At 2 years, an increase in hair growth was demonstrated in 66% of men treated with PROPECIA, compared with 7% of men treated with placebo. At 5 years, 48% of men treated with PROPECIA demonstrated an increase in hair growth, 42% were rated as having no change (no further visible progression of hair loss from baseline) and 10% were rated as having lost hair when compared to baseline. In comparison, 6% of men treated with placebo demonstrated an increase in hair growth, 19% were rated as having no change and 75% were rated as having lost hair when compared to baseline.

A 48-week, placebo-controlled study designed to assess by phototrichogram the effect of PROPECIA on total and actively growing (anagen) scalp hairs in vertex baldness enrolled 212 men with androgenetic alopecia. At baseline and 48 weeks, total and anagen hair counts were obtained in a 1-cm^2 target area of the scalp. Men treated with PROPECIA showed increases from baseline in total and anagen hair counts of 7 hairs and 18 hairs, respectively, whereas men treated with placebo had decreases of 10 hairs and 9 hairs, respectively. These changes in hair counts resulted in a between-group difference of 17 hairs in total hair count (p<0.001) and 27 hairs in anagen hair count (p<0.001), and an improvement in the proportion of anagen hairs from 62% at baseline to 68% for men treated with PROPECIA.

Study in Men with Hair Loss in the Anterior Mid-Scalp Area

A study of 12-month duration, designed to assess the efficacy of PROPECIA in men with hair loss in the anterior mid-scalp area, also demonstrated significant increases in hair count compared with placebo. Increases in hair count were accompanied by improvements in patient self-assessment, investigator assessment, and ratings based on standardized photographs. Hair counts were obtained in the anterior mid-scalp area, and did not include the area of bitemporal recession or the anterior hairline.

Summary of Clinical Studies in Men

Clinical studies were conducted in men aged 18 to 41 with mild to moderate degrees of androgenetic alopecia. All men treated with PROPECIA or placebo received a tar-based shampoo (Neutrogena T/Gel® Shampoo) during the first 2 years of the studies. Clinical improvement was seen as early as 3 months in the patients treated with PROPECIA and led to a net increase in scalp hair count and hair regrowth. In clinical studies for up to 5 years, treatment with PROPECIA slowed the further progression of hair loss observed in the placebo group. In general, the difference between treatment groups continued to increase throughout the 5 years of the studies.

Ethnic Analysis of Clinical Data from Men

In a combined analysis of the two studies on vertex baldness, mean hair count changes from baseline were 91 vs -19 hairs (PROPECIA vs placebo) among Caucasians (n=1185), 49 vs -27 hairs among Blacks (n=84), 53 vs -38 hairs among Asians (n=17), 67 vs 5 hairs among Hispanics (n=45) and 67 vs -15 hairs among other ethnic groups (n=20). Patient self-assessment showed improvement across racial groups with PROPECIA treatment, except for satisfaction of the frontal hairline and vertex in Black men, who were satisfied overall.

14.2 Study in Women

In a study involving 137 postmenopausal women with androgenetic alopecia who were treated with PROPECIA (n=67) or placebo (n=70) for 12 months, effectiveness could not be demonstrated. There was no improvement in hair counts, patient self-assessment, investigator assessment, or ratings of standardized photographs in the women treated with PROPECIA when compared with the placebo group [see Indications and Usage (1)].

16 HOW SUPPLIED/STORAGE AND HANDLING

PROPECIA tablets, 1 mg, are tan, octagonal, film-coated convex tablets with "stylized P" logo on one side and PROPECIA on the other. They are supplied as follows:

NDC 78206-152-01 bottles of 30 (with desiccant)
NDC 78206-152-02 PROPAK® bottles of 90 (with desiccant).

Storage and Handling

Store at room temperature, 15-30°C (59-86°F). Keep container closed and protect from moisture.

Women should not handle crushed or broken PROPECIA tablets when they are pregnant or may potentially be pregnant because of the possibility of absorption of finasteride and the subsequent potential risk to a male fetus. PROPECIA tablets are coated and will prevent contact with the active ingredient during normal handling, provided that the tablets are not broken or crushed [see Warnings and Precautions (5.1), Use in Specific Populations (8.1) and Patient Counseling Information (17)].

17 PATIENT COUNSELING INFORMATION

Advise the patient to read the FDA-approved patient labeling (Patient Information).

Exposure of Women — Risk to Male Fetus

Physicians should inform patients that women who are pregnant or may potentially be pregnant should not handle crushed or broken PROPECIA tablets because of the possibility of absorption of finasteride and the subsequent potential risk to a male fetus. PROPECIA tablets are coated and will prevent contact with the active ingredient during normal handling, provided that the tablets have not been broken or crushed. If a woman who is pregnant or may potentially be pregnant comes in contact with crushed or broken PROPECIA tablets, the contact area should be washed immediately with soap and water [see Contraindications (4), Warnings and Precautions (5.1), Use in Specific Populations (8.1) and How Supplied/Storage and Handling (16)].

Increased Risk of High-Grade Prostate Cancer

Patients should be informed that there was an increase in high-grade prostate cancer in men treated with 5α-reductase inhibitors indicated for BPH treatment, compared to those treated with placebo in studies looking at the use of these drugs to prevent prostate cancer [see Warnings and Precautions (5.3) and Adverse Reactions (6.1)].

Sexual Adverse events

Physicians should inform the patients that PROPECIA may cause symptoms of sexual dysfunction such as decreased libido, erectile dysfunction, and ejaculation disorder, including decreased ejaculate volume.

Additional Instructions

Physicians should instruct their patients to promptly report any changes in their breasts such as lumps, pain or nipple discharge. Breast changes including breast enlargement, tenderness and neoplasm have been reported [see Adverse Reactions (6.1)].

Physicians should instruct their patients to read the patient package insert before starting therapy with PROPECIA and to read it again each time the prescription is renewed so that they are aware of current information for patients regarding PROPECIA.

Dist. by: Organon LLC, a subsidiary of
ORGANON & Co.,
Jersey City, NJ 07302, USA

For patent information: www.organon.com/our-solutions/patent/

The trademarks depicted herein are owned by their respective companies.

© 2022 Organon group of companies. All rights reserved.

uspi-og0906-1t-2208r002

Patient Information
PROPECIA (Pro-pee-sha)
(finasteride)
Tablets

PROPECIA® is for use by MEN ONLY and should NOT be used by women or children.

Read this Patient Information before you start taking PROPECIA and each time you get a refill. There may be new information. This information does not take the place of talking with your healthcare provider about your medical condition or treatment.

What is PROPECIA?

PROPECIA is a prescription medicine used for the treatment of male pattern hair loss (androgenetic alopecia).

It is not known if PROPECIA works for a receding hairline on either side of and above your forehead (temporal area).
PROPECIA is not for use by women and children.

Who should not take PROPECIA?

Do not take PROPECIA if you:

- are pregnant or may become pregnant. PROPECIA may harm your unborn baby.
  - PROPECIA tablets are coated and will prevent contact with the medicine during handling, as long as the tablets are not broken or crushed. Females who are pregnant or who may become pregnant should not come in contact with broken or crushed PROPECIA tablets. If a pregnant woman comes in contact with crushed or broken PROPECIA tablets, wash the contact area right away with soap and water. If a woman who is pregnant comes into contact with the active ingredient in PROPECIA, a healthcare provider should be consulted.
  - If a woman who is pregnant with a male baby swallows or comes in contact with the medicine in PROPECIA, the male baby may be born with sex organs that are not normal.
- are allergic to any of the ingredients in PROPECIA. See the end of this leaflet for a complete list of ingredients in PROPECIA.

What should I tell my healthcare provider before taking PROPECIA?

Before taking PROPECIA, tell your healthcare provider if you:

- have any other medical conditions, including problems with your prostate or liver

Tell your healthcare provider about all the medicines you take, including prescription and non-prescription medicines, vitamins, and herbal supplements.

Know the medicines you take. Keep a list of them to show your healthcare provider and pharmacist when you get a new medicine.

How should I take PROPECIA?

- Take PROPECIA exactly as your healthcare provider tells you to take it.
- You may take PROPECIA with or without food.
- If you forget to take PROPECIA, do not take an extra tablet. Just take the next tablet as usual.

PROPECIA will not work faster or better if you take it more than once a day.

What are the possible side effects of PROPECIA?

- decrease in your blood Prostate Specific Antigen (PSA) levels. PROPECIA can affect a blood test called PSA (Prostate-Specific Antigen) for the screening of prostate cancer. If you have a PSA test done you should tell your healthcare provider that you are taking PROPECIA because PROPECIA decreases PSA levels. Changes in PSA levels will need to be evaluated by your healthcare provider. Any increase in follow-up PSA levels from their lowest point may signal the presence of prostate cancer and should be evaluated, even if the test results are still within the normal range for men not taking PROPECIA. You should also tell your healthcare provider if you have not been taking PROPECIA as prescribed because this may affect the PSA test results. For more information, talk to your healthcare provider.
- There may be an increased risk of a more serious form of prostate cancer in men taking finasteride at 5 times the dose of PROPECIA.

The most common side effects of PROPECIA include:

- decrease in sex drive
- trouble getting or keeping an erection
- a decrease in the amount of semen

The following have been reported in general use with PROPECIA:

- breast tenderness and enlargement. Tell your healthcare provider about any changes in your breasts such as lumps, pain or nipple discharge.
- depression;
- suicidal thoughts;
- decrease in sex drive that continued after stopping the medication;
- allergic reactions including rash, itching, hives and swelling of the lips, tongue, throat, and face;
- problems with ejaculation that continued after stopping medication;
- testicular pain;
- blood in semen;
- difficulty in achieving an erection that continued after stopping the medication;
- male infertility and/or poor quality of semen.
- in rare cases, male breast cancer.

Tell your healthcare provider if you have any side effect that bothers you or that does not go away.

These are not all the possible side effects of PROPECIA. For more information, ask your healthcare provider or pharmacist.

Call your doctor for medical advice about side effects. You may report side effects to FDA at 1-800-FDA-1088.

How should I store PROPECIA?

- Store PROPECIA at room temperature between 59°F to 86°F (15°C to 30°C).
- Keep PROPECIA in a closed container and keep PROPECIA tablets dry (protect from moisture).

Keep PROPECIA and all medicines out of the reach of children.

General information about the safe and effective use of PROPECIA.

Medicines are sometimes prescribed for purposes other than those listed in this Patient Information leaflet. Do not use PROPECIA for a condition for which it was not prescribed. Do not give PROPECIA to other people, even if they have the same symptoms you have. It may harm them.

This Patient Information leaflet summarizes the most important information about PROPECIA. If you would like more information, talk with your healthcare provider. You can ask your pharmacist or healthcare provider for information about PROPECIA that is written for health professionals. For more information, call 1-844-674-3200.

What are the ingredients in PROPECIA?

Active ingredient: finasteride.

Inactive ingredients: lactose monohydrate, microcrystalline cellulose, pregelatinized starch, sodium starch glycolate, hydroxypropyl methylcellulose, hydroxypropyl cellulose, titanium dioxide, magnesium stearate, talc, docusate sodium, yellow ferric oxide, and red ferric oxide.

This Patient Information has been approved by the U.S. Food and Drug Administration.

Dist. by: Organon LLC, a subsidiary of
ORGANON & Co.,
Jersey City, NJ 07302, USA

For patent information: www.organon.com/our-solutions/patent/

© 2023 Organon group of companies. All rights reserved.

Revised: 11/2023

usppi-og0906-1t-2311r002

PRINCIPAL DISPLAY PANEL - 1 mg Tablet Bottle Label

NDC 78206-152-01

Propecia®
(finasteride) Tablets
1 mg

Each tablet contains 1 mg finasteride.
Warning: PROPECIA® (finasteride) should
not be used by women or children. Women
who are or may potentially be pregnant
must not use PROPECIA. They should also
not handle crushed or broken tablets of
PROPECIA. (See Package Insert.)

Rx only

30 Tablets